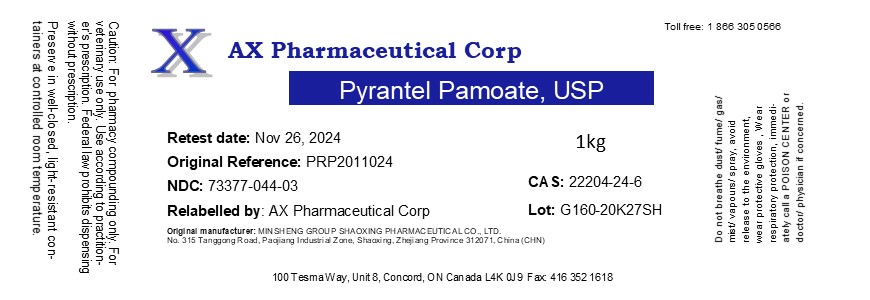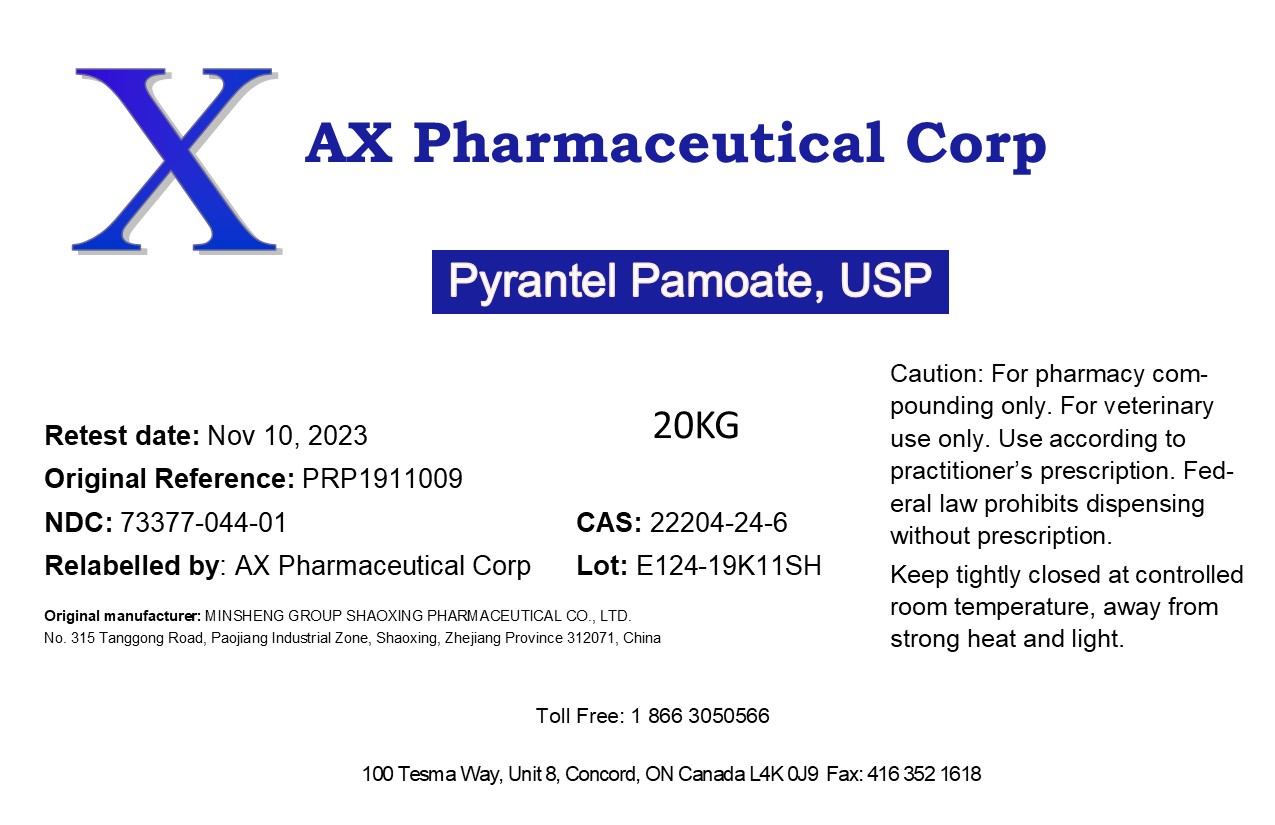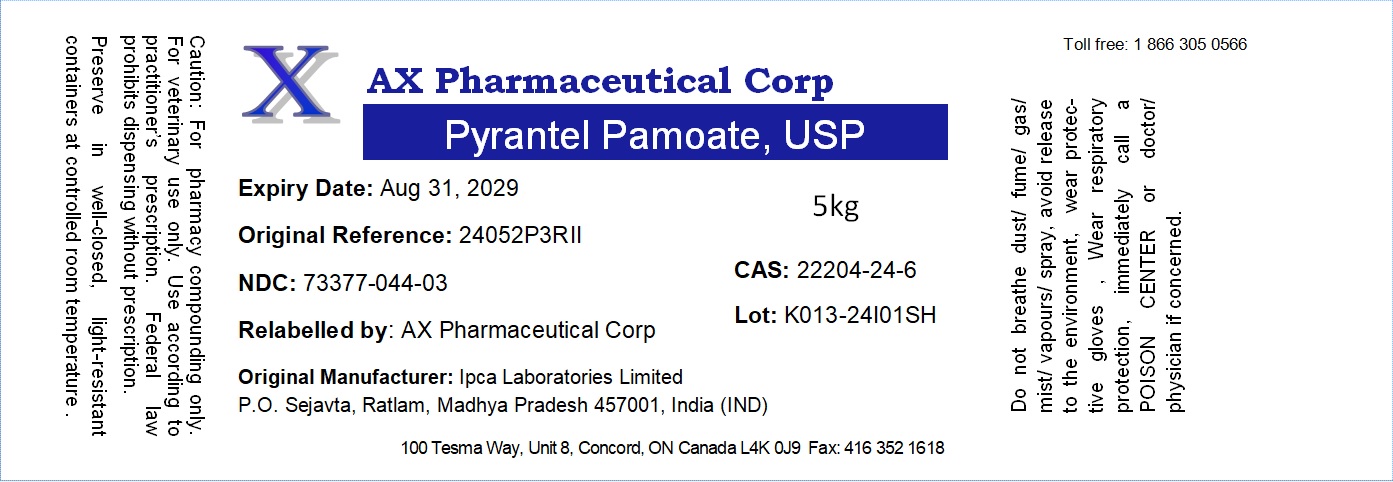 DRUG LABEL: Pyrantel Pamoate
NDC: 73377-044 | Form: POWDER
Manufacturer: AX Pharmaceutical Corp
Category: other | Type: BULK INGREDIENT - ANIMAL DRUG
Date: 20260116

ACTIVE INGREDIENTS: PYRANTEL PAMOATE 1 kg/1 kg

Pyrantel Pamoate